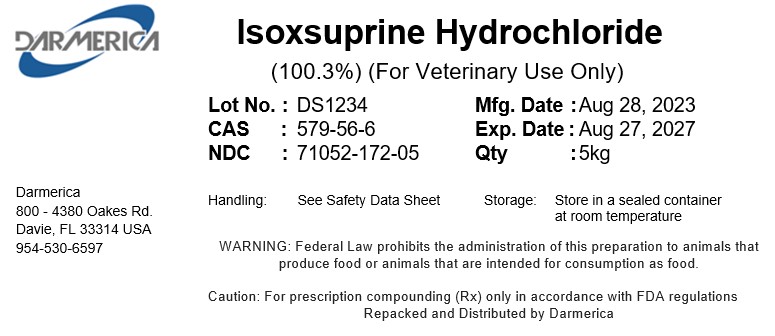 DRUG LABEL: Isoxsuprine Hydrochloride
NDC: 71052-172 | Form: POWDER
Manufacturer: Darmerica, LLC
Category: other | Type: BULK INGREDIENT - ANIMAL DRUG
Date: 20251229

ACTIVE INGREDIENTS: ISOXSUPRINE HYDROCHLORIDE 1 kg/1 kg

Isoxsuprine Hydrochloride